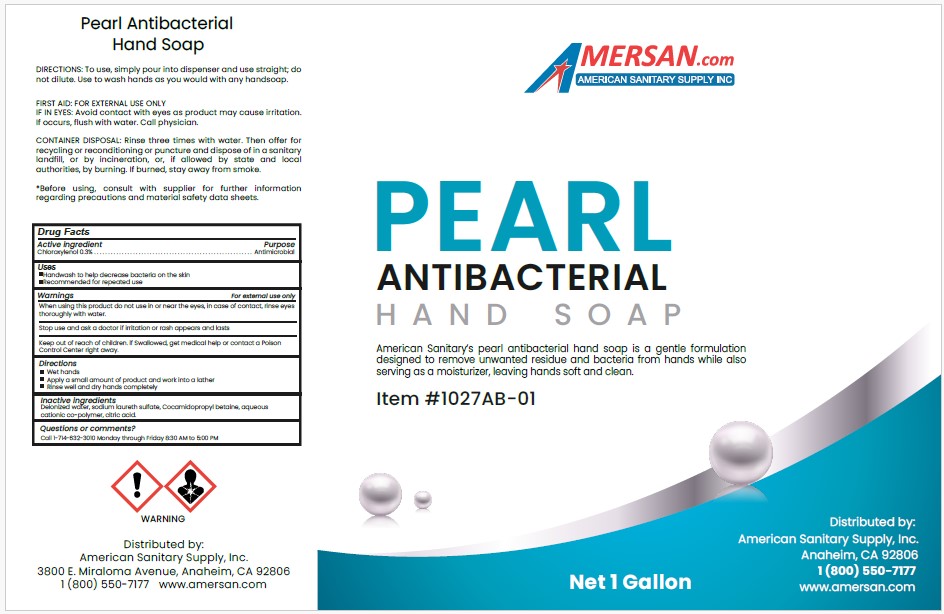 DRUG LABEL: PEARL ANTIMICROBIAL HAND

NDC: 50536-127 | Form: SOAP
Manufacturer: AMERICAN CHEMICAL AND SANITARY SUPPLY INC
Category: otc | Type: HUMAN OTC DRUG LABEL
Date: 20250423

ACTIVE INGREDIENTS: CHLOROXYLENOL 0.3 g/100 mL
INACTIVE INGREDIENTS: WATER; SODIUM LAURETH SULFATE; COCAMIDOPROPYL BETAINE; POLYQUATERNIUM-7 (70/30 ACRYLAMIDE/DADMAC; 1600 KD); ANHYDROUS CITRIC ACID

ACSS (as PLD) - PEARL ANTIMICROBIAL HAND SOAP, ITEM 1027AB-01 (50536-127)

ACTIVE INGREDIENT

CHLOROXYLENOL 0.3%

PURPOSE

ANTIMICROBIAL

USES

- HANDWASH TO HELP DECREASE BACTERIA ON THE SKIN.
- RECOMMENDED FOR REPEATED USE.

WARNINGS

FOR EXTERNAL USE ONLY.

WHEN USING THIS PRODUCT DO NOT USE IN OR NEAR THE EYES. IN CASE OF CONTACT, RINSE EYES THOROUGHLY WITH WATER.

STOP USE AND ASK A DOCTOR IF IRRITATION OR RASH APPEARS AND LASTS.

KEEP OUT OF REACH OF CHILDREN. IF SWALLOWED, GET MEDICAL HELP OR CONTACT A POISON CONTROL CENTER RIGHT AWAY.

DIRECTIONS

- WET HANDS
- APPLY A SMALL AMOUNT OF PRODUCT AND WORK INTO A LATHER
- RINSE WELL AND DRY HANDS COMPLETELY

INACTIVE INGREDIENTS

DEIONIZED WATER, SODIUM LAURETH SULFATE, COCAMIDOPROPYL BETAINE, AQUEOUS CATIONIC CO-POLYMER, CITRIC ACID.